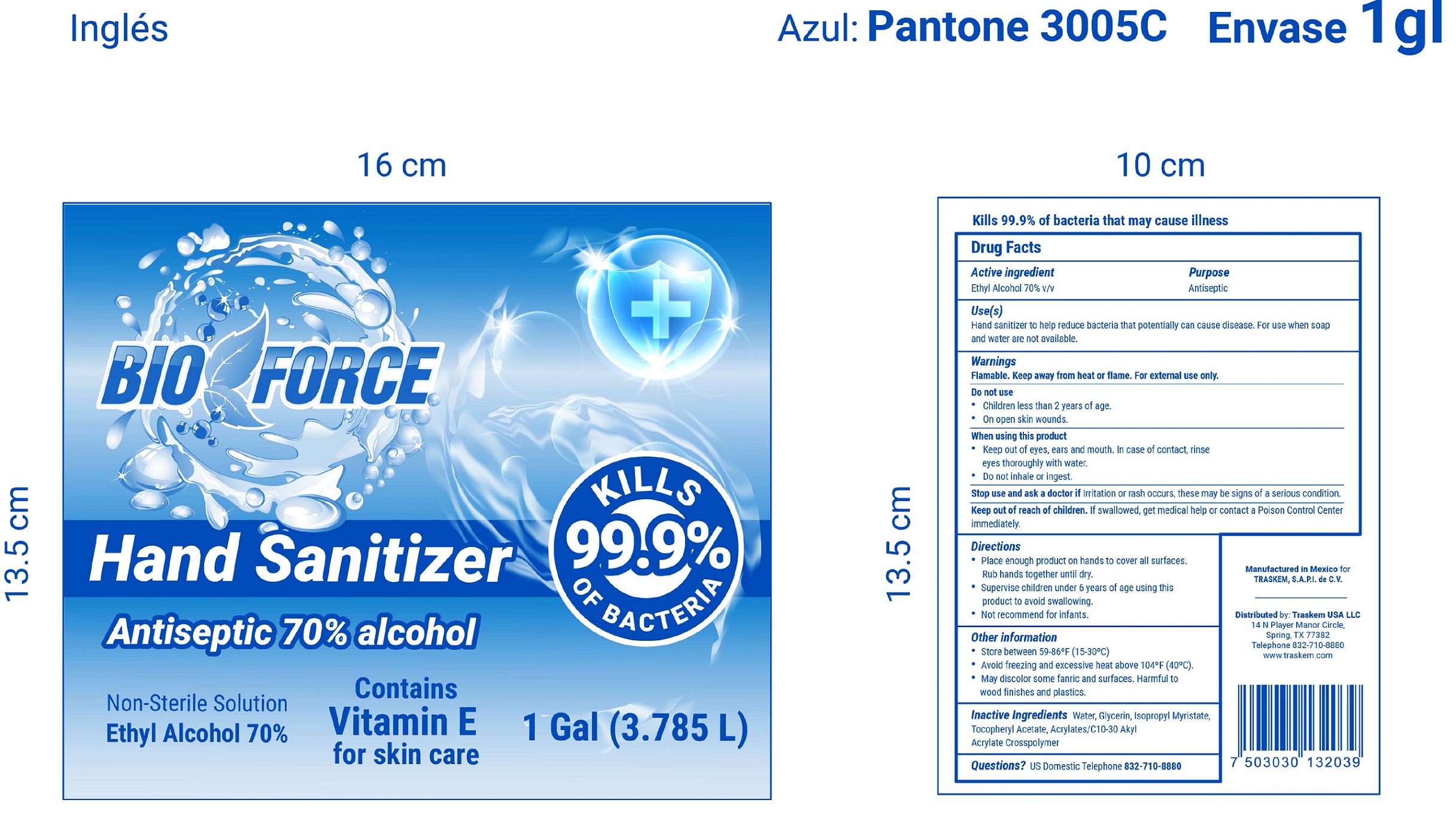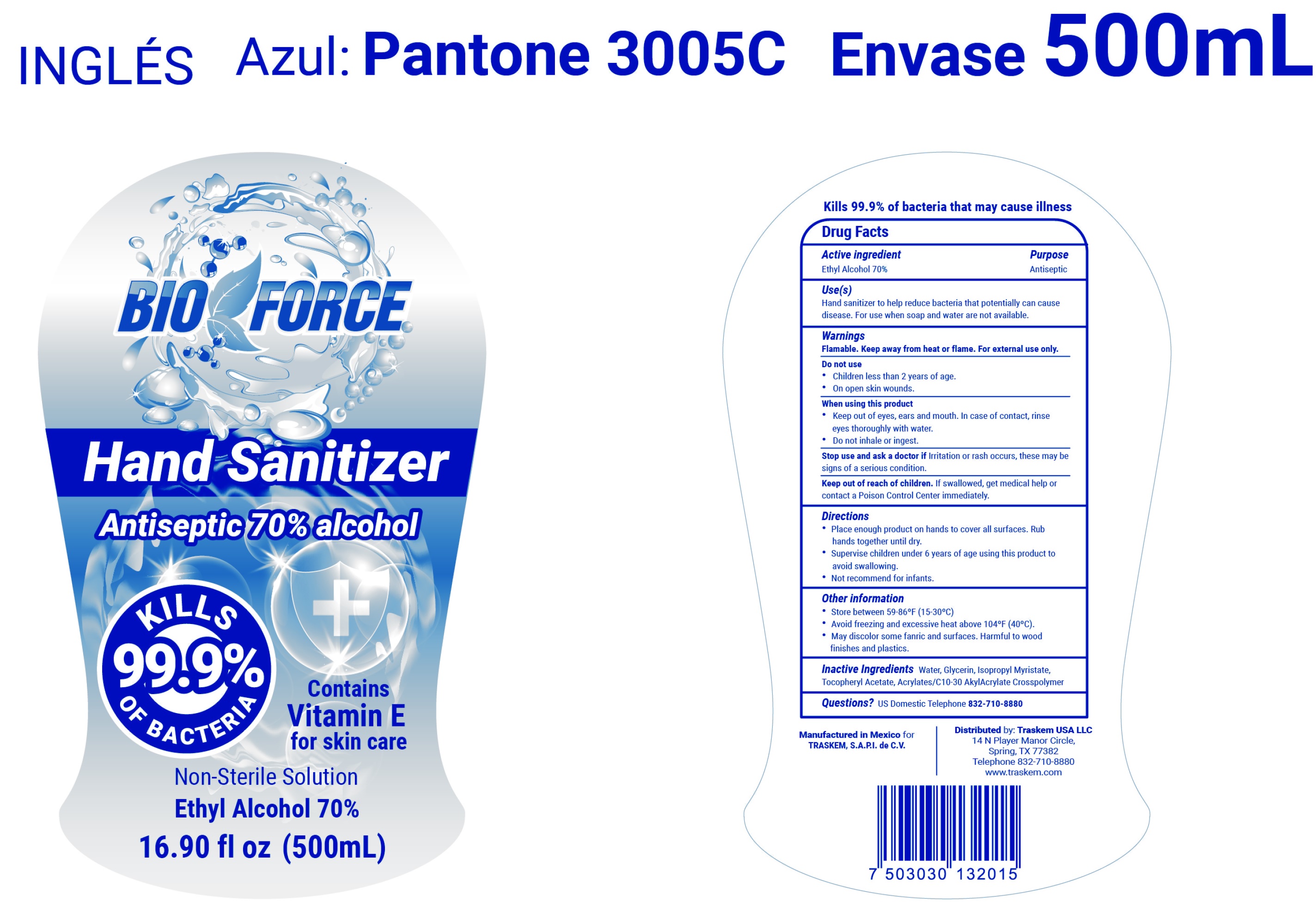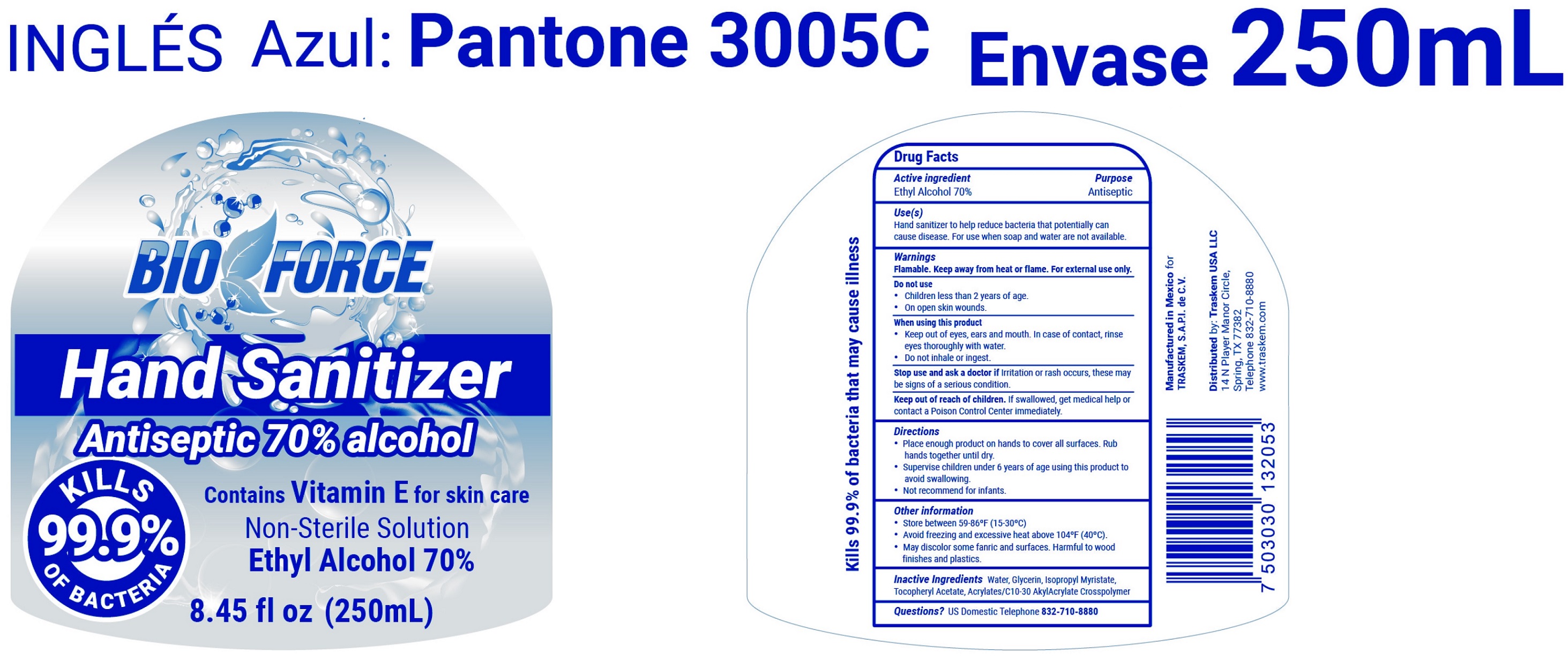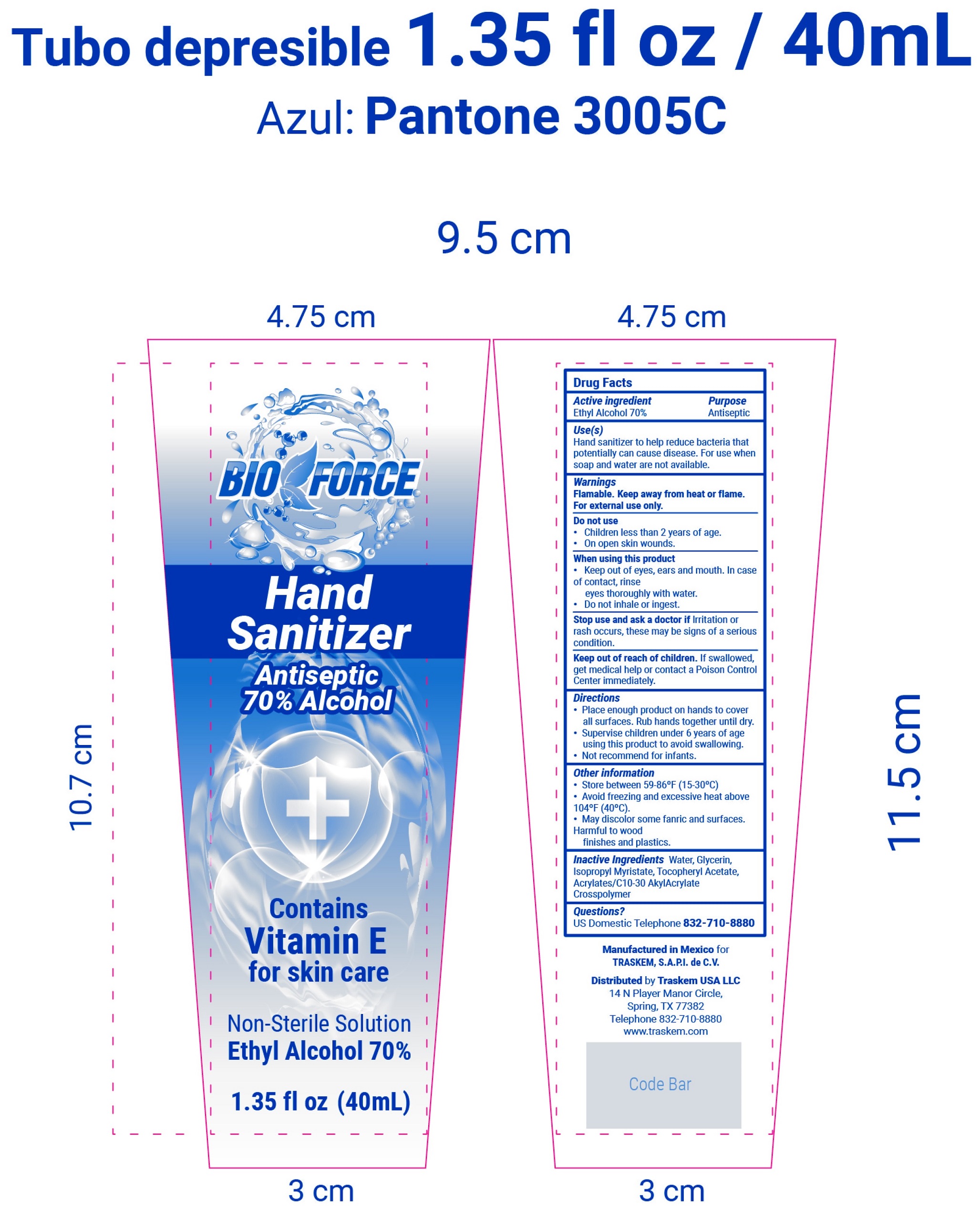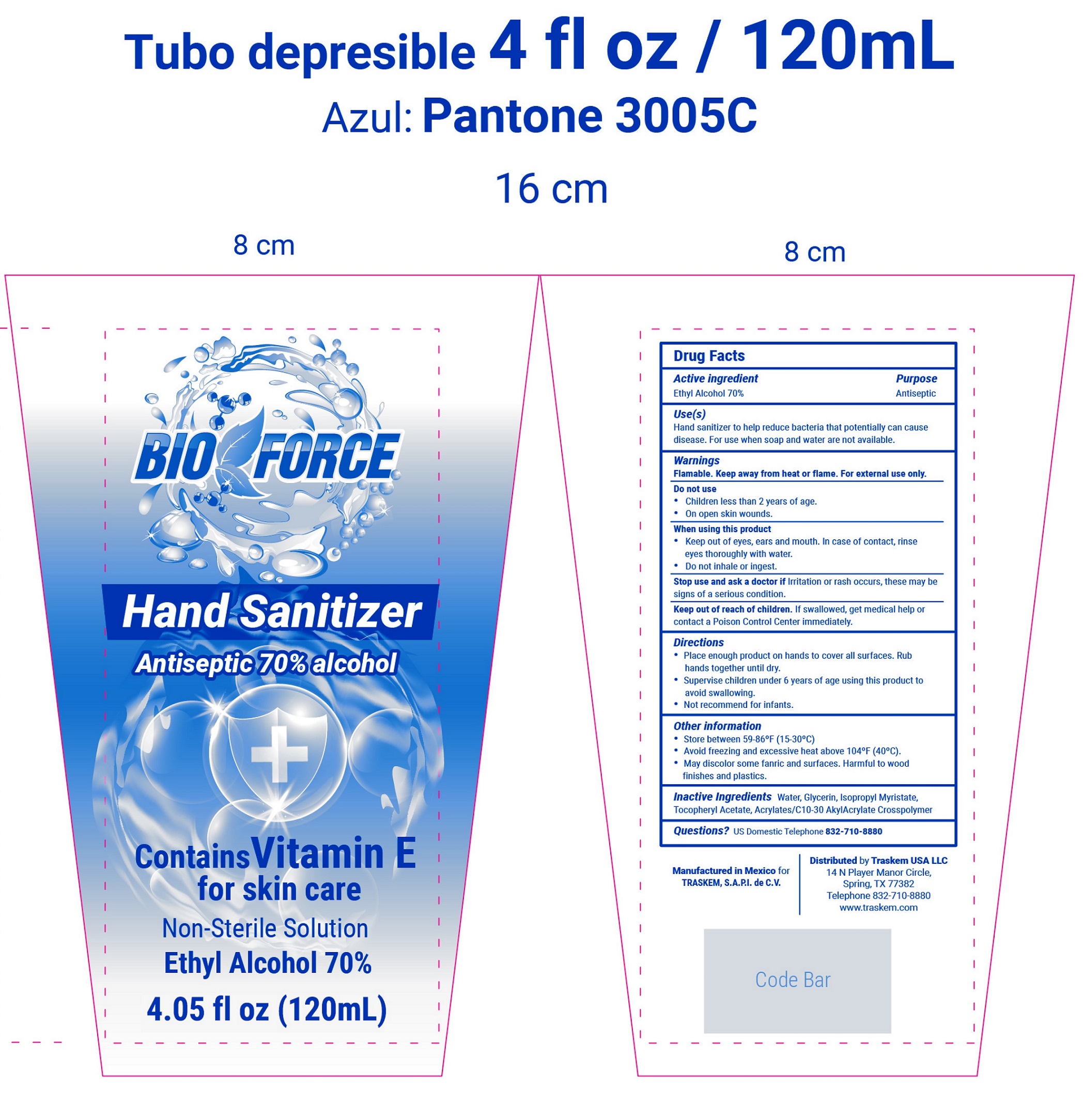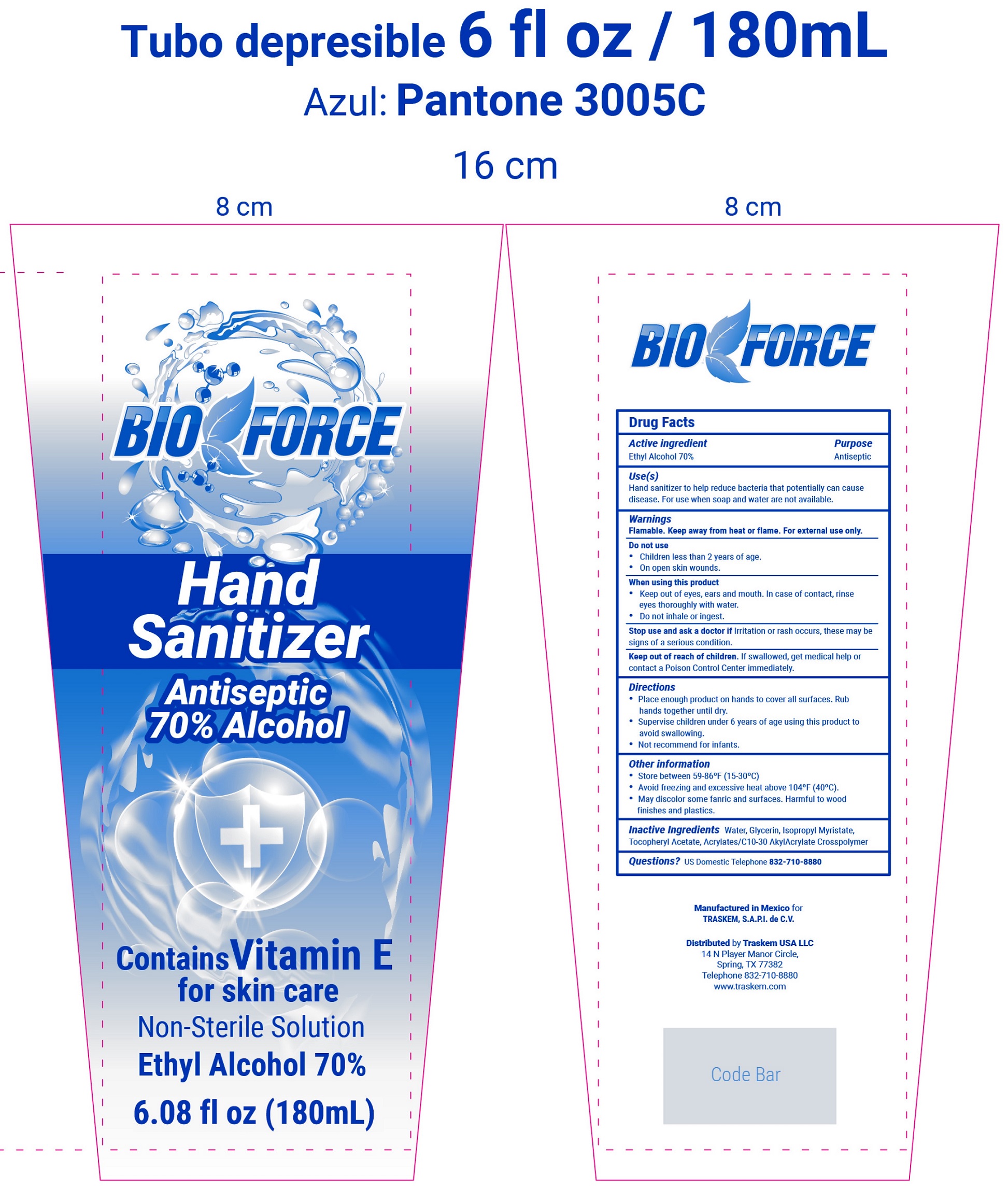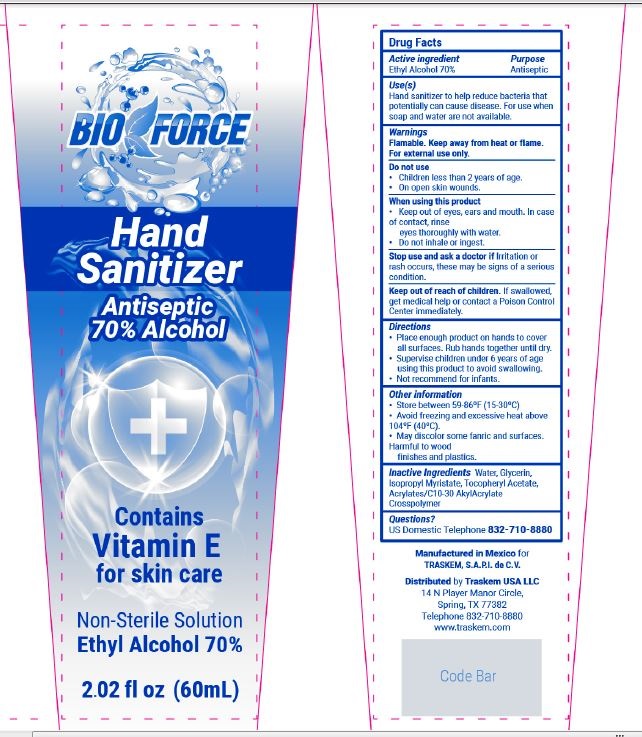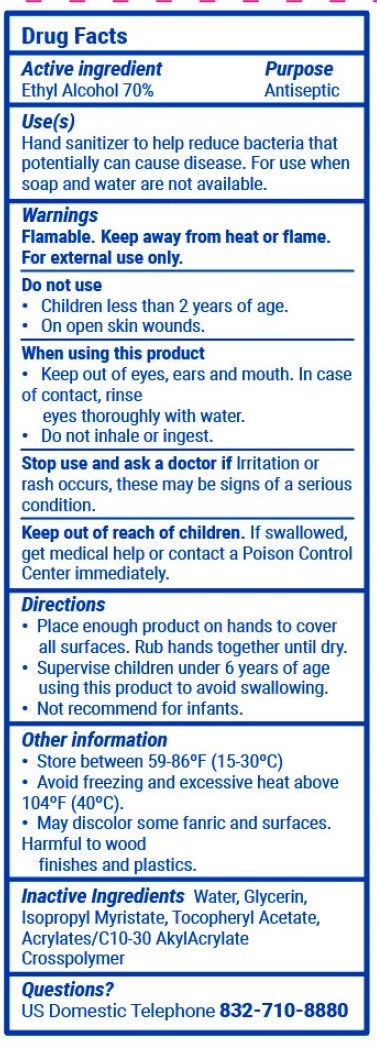 DRUG LABEL: Bio Force Hand Sanitizer 70%
NDC: 80154-000 | Form: GEL
Manufacturer: TRASKEM SAPI de CV
Category: otc | Type: HUMAN OTC DRUG LABEL
Date: 20200924

ACTIVE INGREDIENTS: ALCOHOL 0.7 mL/1 mL
INACTIVE INGREDIENTS: WATER; GLYCERIN; ISOPROPYL MYRISTATE; .ALPHA.-TOCOPHEROL ACETATE; CARBOMER INTERPOLYMER TYPE A (ALLYL SUCROSE CROSSLINKED)

Bio Force Hand Sanitizer 70%

Active ingredients

Ethyl Alcohol 70% v/v

Purpose

Antiseptic

Use(s)

Hand santizer to help reduce bacteia that potentially can cause disease. For use when soap and water are not available.

Warnings

Flamable. Keep away from heat or flame. For external use only.

Do not us

- Children less than 2 years of age.
- On open skin wounds.

When using this product

- Keep out of eyes, ears and mouth. In case of contact, rinse eyes thoroughly with water.
- Do not inhale of ingest.

Stop use and ask a doctor if

irritation or rash occurs, these may be signs of a serious condition.

Keep out of reach of children.

If swallowed, get medical help or contact a Poison Control center immediately.

Directions

- Place enough product on hands to cover all surfaces. Rub hands together until dry.
- Supervise children under 6 years of age using this product to avoid swallowing.
- Not recommended for infants.

Other inforamtion

- Store between 59-86°F (15-30°C)
- Avoid freezing and excessive heat above 104°F (40°C).
- May discolor some fanric and surfaces. Harmful to wood finishes and plastics.

Inactive Ingredients

Water, Glycerin, Isopropyl Myristate, Tocopheryl Acetate, Acrylates/C10-30 Akly Acrylate Crosspolymer

Questions?

US Domestic Telephone 832-710-8880